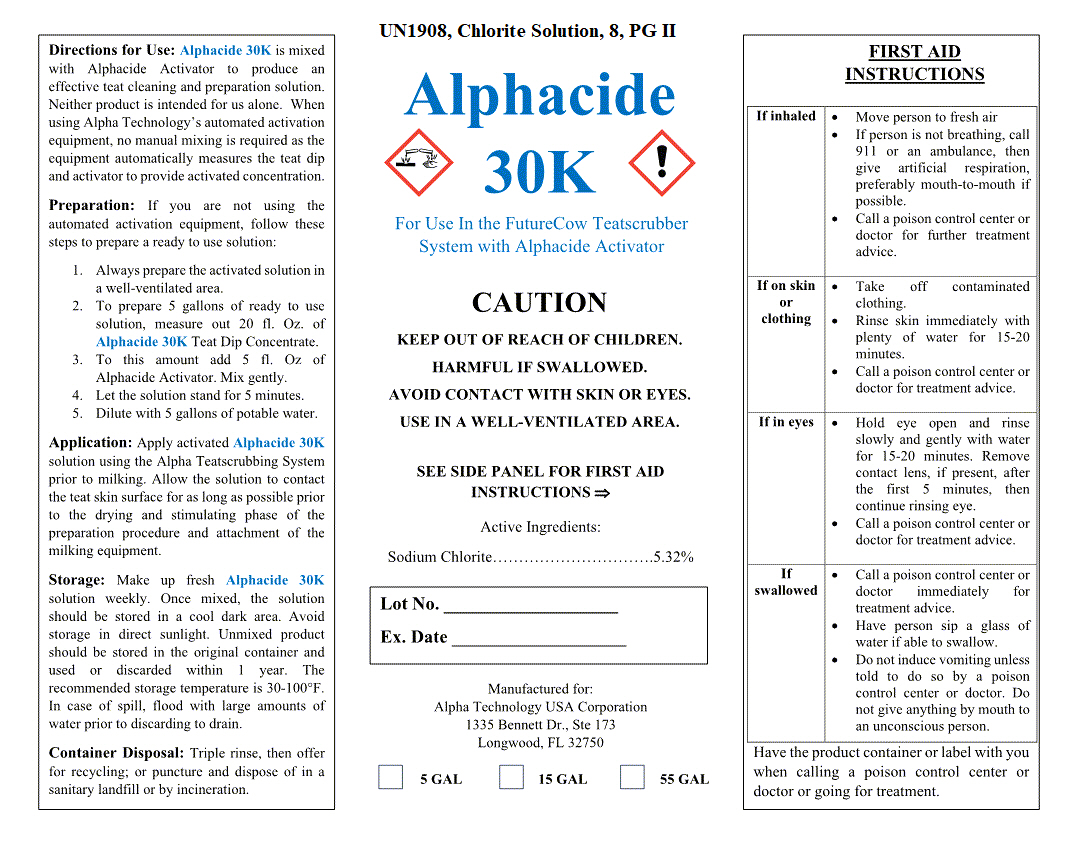 DRUG LABEL: Alphacide 30K
NDC: 33642-9410 | Form: SOLUTION
Manufacturer: Alpha Technology USA Corp
Category: animal | Type: OTC ANIMAL DRUG LABEL
Date: 20190819

ACTIVE INGREDIENTS: SODIUM CHLORITE 0.1743 kg/1 kg
INACTIVE INGREDIENTS: WATER 0.8257 kg/1 kg

Alphacide 30K

DESCRIPTION

Alphacide 30K

For Use in the FutureCow Teatscrubber System with Alphacide Activator

WARNINGS AND PRECAUTIONS

CAUTION

KEEP OUT OF REACH OF CHILDREN. HARMFUL IF SWALLOWED.

AVOID CONTACT WITH SKIN OR EYES.

USE IN A WELL-VENTILATED AREA.

SEE SIDE PANEL FOR FIRST AID INSTRUCTIONS

Active Ingredients:

Sodium Chlorite.................................5.32%

Manufactured for:

Alpha Technology USA Corporation 1335 Bennett Dr., Ste 173

Longwood, FL 32750

UN1908, Chlorite Solution, 8, PG II

_ 5 Gal _15 Gal _55 Gal _ 265 Gal

OTHER SAFETY INFORMATION

FIRST AID INSTRUCTIONS

If inhaled - Move person to fresh air. If person is not breathing, call 911 or an ambulance, then give artificial respiration, preferably mouth-to-mouth if possible. Call a poison control center or doctor for further treatment advice.

If on skin or clothing - Take off contaminated clothing. Rinse skin immediately with plenty of water for 15-20 minutes. Call a poison control center or doctor for treatment advice.

If in eyes - Hold eye open and rinse slowly and gently with water for 15-20 minutes. Remove contact lens, if present, after the first 5 minutes, then continue rinsing eye. Call a poison control center or doctor for treatment advice.

If swallowed - Call a poison control center or doctor immediately for treatment advice. Have person sip a glass of water if able to swallow . Do not induce vomiting unless told to do so by a poison control center or doctor. Do not give anything by mouth to an unconscious person.

Have the product container or label with you when calling a poison control center or doctor or going for treatment.

INSTRUCTIONS FOR USE

Directions for Use: : Alphacide 30K is mixed with Alphacide Activator to produce an effective teat cleaning and preparation solution. Neither product is intended for use alone. When using Alpha Technology's automated activation equipment, no manual mixing is required as the equipment automatically measures the teat dip and activator to provide activated concentrate .

Preparation: If you are not using the automated activation equipment, follow these steps to prepare a ready to use solution :

1. Always prepare the activated solution in a well-ventilated area .
2. To prepare 5 gallons of ready to use solution, measure out 20 fl. Oz. of Alphacide 30K Teat Dip Concentrate.
3. To this amount add 5 fl. oz. of Alphacide Activator. Mix gently.
4. Let the solution stand for 5 minutes.
5. Dilute with 5 gallons of potable water .

Application: Apply activated Alphacide 30K Solution using the Alpha Teat Scrubbing System prior to milking. Allow the solution to contact the teat skin surface for as long as possible prior to the drying and stimulating phase of the preparation procedure and attachment of the milking equipment .

Storage: Make up fresh Alphacide 20K solutions weekly. Once mixed, the solution should be stored in a coo l dark area. Avoid storage in direct sunlight. Unmixed product should be stored in the original container and used or discarded within 1 year. The recommended storage temperature is 30-100° F. In case of spi ll, flood with large amounts of water prior to discarding to drain

Container Disposal: Triple rinse, then offer for recycling; or puncture and dispose of in a sanitary landfill or by incineration .